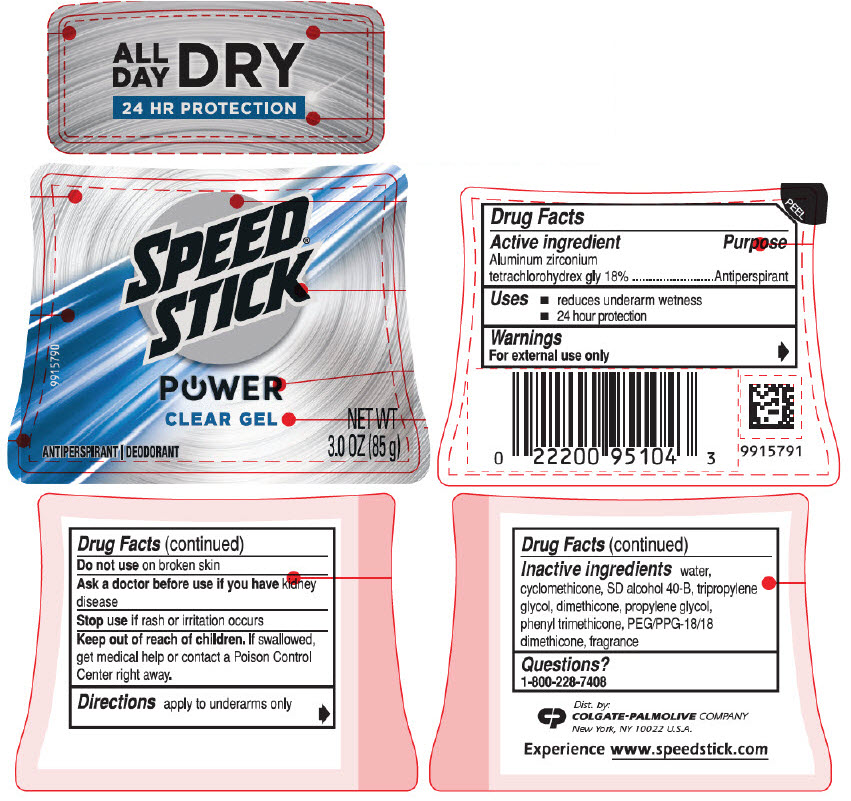 DRUG LABEL: Speed Stick
NDC: 35000-854 | Form: STICK
Manufacturer: Colgate-Palmolive Company
Category: otc | Type: HUMAN OTC DRUG LABEL
Date: 20200110

ACTIVE INGREDIENTS: ALUMINUM ZIRCONIUM TETRACHLOROHYDREX GLY 180 mg/1 g
INACTIVE INGREDIENTS: WATER; CYCLOMETHICONE; DIMETHICONE; PROPYLENE GLYCOL; PHENYL TRIMETHICONE; PEG/PPG-18/18 DIMETHICONE

Speed
stick® Gel
POWER™
ULTIMATE SPORT

Drug Facts

Active ingredient

Aluminum zirconium tetrachlorohydrex gly 18%

Purpose

Antiperspirant

Uses

- reduces underarm wetness
- extra effective

Warnings

For external use only

Do not use on broken skin

Ask a doctor before use if you have kidney disease

Stop use if rash or irritation occurs

Keep out of reach of children. If swallowed, get medical help or contact a Poison Control Center right away.

Directions

- apply to underarms only
- turn dial to raise product

Inactive ingredients

water, cyclomethicone, SD alcohol 40-B, tripropylene glycol, dimethicone, propylene glycol, phenyl trimethicone, PEG/PPG-18/18 dimethicone, fragrance

Questions?

1-800-228-7408

Dist. by:
COLGATE-PALMOLIVE COMPANY
New York, NY 10022

PRINCIPAL DISPLAY PANEL - 85 g Container Label

ALL
DAY
DRY

24 HR PROTECTION

SPEED®
STICK

POWER
CLEAR GEL

9915790

ANTIPERSPIRANT | DEODORANT
NET WT
3.0 OZ (85 g)